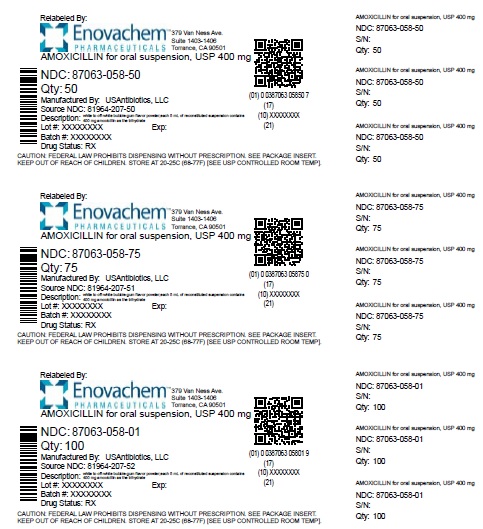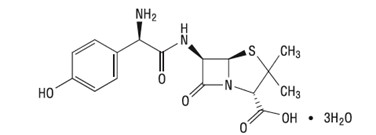 DRUG LABEL: Amoxicillin
NDC: 87063-058 | Form: FOR SUSPENSION
Manufacturer: ASCLEMED USA INC.
Category: prescription | Type: HUMAN PRESCRIPTION DRUG LABEL
Date: 20251210

ACTIVE INGREDIENTS: AMOXICILLIN 400 mg/5 mL
INACTIVE INGREDIENTS: SILICON DIOXIDE; SODIUM BENZOATE; SODIUM CITRATE; SUCROSE; XANTHAN GUM

HIGHLIGHTS OF PRESCRIBING INFORMATION

These highlights do not include all the information needed to use AMOXICILLIN safely and effectively. See full prescribing information for AMOXICILLIN.
AMOXICILLIN for oral suspension
Initial U.S. Approval: 1974

RECENT MAJOR CHANGES

Warnings and Precautions, Drug-Induced Enterocolitis Syndrome (DIES) (5.3) | 05/2024

1. INDICATIONS AND USAGE

AMOXICILLIN is a penicillin-class antibacterial indicated for treatment of infections due to susceptible strains of designated microorganisms.(1)

Adults and Pediatric Patients (1)

- Upper Respirtory Tract Infections of the Ear, Nose, and Throat
- Infections of the Genitourinary Tract
- Infections of the Skin and Skin Structure
- Infections of the Lower Respiratory Tract

Adults Patients only (1)

- Helicobacter pyloriInfection and Duodenal Ulcer Disease

Usage:

To reduce the development of drug-resistant bacteria and maintain the effectiveness of amoxicillin and other antibacterial drugs, amoxicillin should be used only to treat or prevent infections that are proven or strongly suspected to be caused by bacteria. (1)

2 DOSAGE AND ADMINISTRATION

- In Adults, 750-1750 mg/day in divided doses every 8 to 12 hours.
- In Pediatric Patients over 3 Months of Age, 20 to 45 mg/kg/day in divided doses every 8 to 12 hours. Refer to full prescribing information for specific dosing regimens. (2.2, 2.3)
- The upper dose for neonates and infants age 3 months or younger is 30 mg/kg/day divided every 12 hours. (2.3)
- Dosing for H. pyloriInfection (in Adults): Triple therapy: 1 gram amoxicillin, 500 mg clarithromycin, and 30 mg lansoprazole, all given twice daily (every 12 hours) for 14 days. Dual therapy: 1 gram amoxicillin and 30 mg lansoprazole, each given three times daily (every 8 hours) for 14 days. (2.4)
- Reduce the dose in patients with severe renal impairment (GFR greater than 30 mL/min). (2.5)

3 DOSAGE FORMS AND STRENGTHS

- Tablets: 500 mg, 875 mg (3)
- For Oral Suspension: 200 mg/5 mL, 400 mg/5 mL (3)
- Chewable Tablets:125 mg, 200 mg, 250 mg, 400 mg (3)

4 CONTRAINDICATIONS

- History of a serious hypersensitivity reaction (e.g., anaphylaxis or Stevens-Johnson syndrome) to Amoxicillin or to other beta-lactams (e.g., penicillins or cephalosporins). (4)

5 WARNINGS AND PRECAUTIONS

- Anaphylactic reactions: Serious and occasionally fatal anaphylactic reactions have been reported in patients on penicillin therapy, including amoxicillin. Discontinue Amoxicillin if a reaction occurs (5.1).
- Severe cutaneous adverse reactions (SCAR): Monitor closely. Discontinue if rash progresses. (5.2)
- Drug-induced enterocolitis syndrome (DIES) has been reported with amoxicillin use. If this occurs, discontinue Amoxicillin and institute appropriate therapy. (5.3)
- Clostridioidesdifficile-associated diarrhea (CDAD)(ranging from mild diarrhea to fatal colitis): Evaluate if diarrhea occurs. (5.4)

6 ADVERSE REACTIONS

The most common adverse reactions (greater than 1%) observed in clinical trials of amoxicillin tablets or oral suspension were diarrhea, rash, vomiting, and nausea. (6.1)

To report SUSPECTED ADVERSE REACTIONS, contact USAntibiotics, LLC at 1-844-454-5532 or FDA at 1-800-FDA-1088 or www.fda.gov/medwatch

7 DRUG INTERACTIONS

- Co-administration with probenicid is not recommended. (7.1)
- Concomitant use of amoxicillin and oral anticoagulants may increase the prolongation of prothrombin time. (7.2)
- Co-administration with allopurinol increases the risk of rash. (7.3)
- Amoxicillin may reduce the efficacy of oral contraceptives. (7.4)

FULL PRESCRIBING INFORMATION

1. INDICATIONS AND USAGE

Adults and Pediatric Patients

- Upper Respiratory Tract Infectionsofthe Ear, Nose, and Throat:Amoxicillin is indicated in the treatment of infections due to susceptible (ONLY β-lactamase–negative) isolates of Streptococcusspecies. (α-and β-hemolytic isolates only), Streptococcus pneumoniae, Staphylococcusspp., or Haemophilus influenzae.

- Infectionsofthe Genitourinary Tract: Amoxicillin is indicated in the treatment of infections due to susceptible (ONLY β-lactamase–negative) isolates of Escherichia coli, Proteus mirabilis, or Enterococcus faecalis.

- Infectionsofthe Skin and Skin Structure:Amoxicillin is indicated in the treatment of infections due to susceptible (ONLY β-lactamase–negative) isolates of Streptococcusspp. (α-and β-hemolytic isolates only), Staphylococcusspp., or E. coli.

- Infectionsofthe Lower Respiratory Tract:Amoxicillin is indicated in the treatment of infections due to susceptible (ONLY β-lactamase–negative) isolates of Streptococcusspp. (α-and β-hemolytic isolates only), S. pneumoniae, Staphylococcusspp., or H. influenzae.

Adults Patients only

- Helicobacter pyloriInfection and Duodenal Ulcer Disease :

Triple therapy for Helicobacter pylori (H. pylori)with clarithromycin and lansoprazole :

Amoxicillin, in combination with clarithromycin plus lansoprazole as triple therapy, is indicated for the treatment of patients with H. pyloriinfection and duodenal ulcer disease (active or 1-year history of a duodenal ulcer) to eradicate H. pylori. Eradication of H. pylorihas been shown to reduce the risk of duodenal ulcer recurrence.

Dual therapy for H. pyloriwith lansoprazole : Amoxicillin, in combination with lansoprazole delayed-release capsules as dual therapy, is indicated for the treatment of patients with H. pyloriinfection and duodenal ulcer disease (active or 1-year history of a duodenal ulcer) who are either allergic or intolerant to clarithromycin or in whom resistance to clarithromycin is known or suspected. (See the clarithromycin package insert, MICROBIOLOGY.) Eradication of H. pylorihas been shown to reduce the risk of duodenal ulcer recurrence.

Usage

To reduce the development of drug-resistant bacteria and maintain the effectiveness of Amoxicillin and other antibacterial drugs, Amoxicillin should be used only to treat infections that are proven or strongly suspected to be caused by bacteria. When culture and susceptibility information are available, they should be considered in selecting or modifying antibacterial therapy. In the absence of such data, local epidemiology and susceptibility patterns may contribute to the empiric selection of therapy.

2 DOSAGE AND ADMINISTRATION

2.1 Important Administration Instructions

To minimize the potential for gastrointestinal intolerance, Amoxicillin should be taken at the start of a meal.

2.2 Dosage for Adults and for Pediatric Patients Aged 3 Months (12 weeks) and Older

- Treatment should be continued for a minimum of 48 to 72 hours beyond the time that the patient becomes asymptomatic, or evidence of bacterial eradication has been obtained.
- It is recommended that there be at least 10 days’ treatment for any infection caused by Streptococcus pyogenesto prevent the occurrence of acute rheumatic fever.
- In some infections, therapy may be required for several weeks. It may be necessary to continue clinical and/or bacteriological follow-up for several months after cessation of therapy.

Table 1. Dosage Recommendations for Adult and Pediatric Patients Aged 3 Months (12 weeks) and Older

Infection | Severitya | Recommended Dosage for; Adults and Pediatric; Patients Aged 3 Months; and Older and Weight; Greater than 40 kg | Recommended Dosage for; Pediatric Patients Aged 3; Months and Older and; Weight Less than 40 kg
Ear/Nose/Throat; Skin/Skin Structure; Genitourinary Tract | Mild/Moderate | 500 mg every 12 hour or; 250 mg every 8 hours | 25 mg/kg/day in divided doses; every 12 hours; or; 20 mg/kg/day in divided doses; every 8 hours
Ear/Nose/Throat; Skin/Skin Structure; Genitourinary Tract | Severe | 875 mg every 12 hours or; 500 mg every 8 hours | 45 mg/kg/day in divided doses; every 12 hours; or; 40 mg/kg/day in divided doses; every 8 hours
Lower Respiratory; Tract | Mild/Moderate or; Severe | 875 mg every 12 hours or; 500 mg every 8 hours | 45 mg/kg/day in divided doses; every 12 hours; or; 40 mg/kg/day in divided doses; every 8 hours

aDosage for infections caused by bacteria that are intermediate in their susceptibility to amoxicillin should follow the recommendations for severe infections.

2.3 Dosage in Pediatric Patients Aged Less than 12 Weeks (3 months)

- It is recommended that there be at least 10 days’ treatment for any infection caused by Streptococcuspyogenesto prevent the occurrence of acute rheumatic fever.

- Due to incompletely developed renal function affecting elimination of amoxicillin in this age group, the recommended upper dose of amoxicillin is 30 mg/kg/day divided every 12 hours. There are currently no dosing recommendations for pediatric patients with impaired renal function.

- Treatment should be continued for a minimum of 48 to 72 hours beyond the time that the patient becomes asymptomatic, or evidence of bacterial eradication has been obtained.

2.4 Dosing for H. pyloriInfection in Adults

Tripletherapy:The recommended adult oral dose is 1 gram amoxicillin, 500 mg clarithromycin, and 30 mg lansoprazole, all given twice daily (every 12 hours) for 14 days.

Dualtherapy:The recommended adult oral dose is 1 gram amoxicillin and 30 mg lansoprazole, each given three times daily (every 8 hours) for 14 days.

Please refer to clarithromycin and lansoprazole full prescribing information.

2.5 Dosing in Renal Impairment for Adults and Pediatric Patients Aged 3 Months and Older and Weight Greater than 40 kg

- Patients with impaired renal function do not generally require a reduction in dose unless the impairment is severe. Renal impairment patients with a glomerular filtration rate of less than 30 mL/min should NOTreceive the 875 mg dose. See dosage regimens in patients with severe renal impairment provided in Table 2.

Table 2. Dosing in Patients with Severe Renal Impairment

Patients with Renal Impairment | Dosage Regimen
GFR 10 to 30 mL/min | 500 mg or 250 mg every 12 hours, depending on the severity of the infection
GFR less than 10 mL/min | 500 mg or 250 mg every 24 hours, depending on severity of the infection
Hemodialysis | 500 mg or 250 mg every 24 hours, depending on severity of the infection; Administer an additional dose both during and at the end of dialysis

2.6 Directions for Mixing Oral Suspension

Prepare a suspension at time of dispensing as follows: Tap bottle until all powder flows freely. Measure the total amount of water (see Table 3). Add approximately 1/3 of the water to powder. Replace cap and shake vigorouslyto wet powder. Add remaining water and again shake vigorously.

Table 3. Amount of Water For Mixing Oral Suspension

Strength | Bottle Size | Total Amount of Water; Required for Reconstitution
For Oral Suspension 200 mg/5 mL | 50 mL | 39 mL
For Oral Suspension 200 mg/5 mL | 75 mL | 57 mL
For Oral Suspension 200 mg/5 mL | 100 mL | 76 mL
For Oral Suspension 400 mg/5 mL | 50 mL | 36 mL
For Oral Suspension 400 mg/5 mL | 75 mL | 54 mL
For Oral Suspension 400 mg/5 mL | 100 mL | 71 mL

After reconstitution, the required amount of suspension should be placed directly on the child's tongue for swallowing. Alternate means of administration are to add the required amount of suspension to formula, milk, fruit juice, water, ginger ale, or cold drinks. These preparations should then be taken immediately.

SHAKE ORAL SUSPENSION WELL BEFORE USING. Keep bottle tightly closed. Any unused portion of the reconstituted suspension must be discarded after 14 days. Refrigeration is preferable, but not required.

3 DOSAGE FORMS AND STRENGTHS

Amoxicillin:

- Tablets: 500 mg, 875 mg. Each tablet contains 500 mg or 875 mg amoxicillin as the trihydrate. Each film-coated, capsule-shaped, pink tablet is debossed with AMOXIL centered over 500 or 875, respectively. The 875-mg tablet is scored on the reverse side.
- For Oral Suspension:200 mg/5 mL, 400 mg/5 mL. Each 5 mL of reconstituted bubble-gum flavored suspension contains 200 mg or 400 mg amoxicillin as the trihydrate.
- Chewable Tablets:
  125 mg – Each 125 mg cherry-banana-peppermint flavored tablet contains 125 mg of amoxicillin as the trihydrate. Each pale pink, oval tablet is imprinted with AMOXIL on one side and 125 on the other.
  200 mg – Each 200 mg cherry-banana-peppermint flavored tablet contains 200 mg of amoxicillin as the trihydrate. Each pale pink, round convex tablet is imprinted with AMOXIL and 200 along the edge of 1 side.
  250 mg – Each 250 mg cherry-banana-peppermint flavored tablet contains 250 mg of amoxicillin as the trihydrate. Each pale pink, oval tablet is imprinted with AMOXIL on one side and 250 on the other.
  400 mg – Each 400 mg cherry-banana-peppermint flavored tablet contains 400 mg of amoxicillin as the trihydrate. Each pale pink, round convex tablet is imprinted with AMOXIL and 400 along the edge of 1 side.

4 CONTRAINDICATIONS

AMOXIL is contraindicated in patients who have experienced a serious hypersensitivity reaction (e.g., anaphylaxis or Stevens-Johnson syndrome) to AMOXIL or to other β-lactam antibacterial drugs (e.g., penicillins and cephalosporins).

5 WARNINGS AND PRECAUTIONS

5.1 Anaphylactic Reactions

Serious and occasionally fatal hypersensitivity (anaphylactic) reactions have been reported in patients on penicillin therapy including amoxicillin. Although anaphylaxis is more frequent following parenteral therapy, it has occurred in patients on oral penicillins. These reactions are more likely to occur in individuals with a history of penicillin hypersensitivity and/or a history of sensitivity to multiple allergens. There have been reports of individuals with a history of penicillin hypersensitivity who have experienced severe reactions when treated with cephalosporins. Before initiating therapy with amoxicillin, careful inquiry should be made regarding previous hypersensitivity reactions to penicillins, cephalosporins, or other allergens. If an allergic reaction occurs, amoxicillin should be discontinued, and appropriate therapy instituted.

5.2 Severe Cutaneous Adverse Reactions

Amoxicillin may cause severe cutaneous adverse reactions (SCAR), such as Stevens-Johnson syndrome (SJS), toxic epidermal necrolysis (TEN), drug reaction with eosinophilia and systemic symptoms (DRESS), and acute generalized exanthematous pustulosis (AGEP). If patients develop skin rash they should be monitored closely, and amoxicillin discontinued if lesions progress.

5.3 Drug-Induced Enterocolitis Syndrome (DIES)

Drug-induced enterocolitis syndrome (DIES) has been reported with amoxicillin use [see Adverse Reactions (6.2)] , with most cases occurring in pediatric patients < 18 years of age. DIES is a non-IgE mediated hypersensitivity reaction characterized by protracted vomiting occurring 1 to 4 hours after drug ingestion in the absence of skin or respiratory symptoms. DIES may be associated with pallor, lethargy, hypotension, shock, diarrhea within 24 hours after ingesting amoxicillin, and leukocytosis with neutrophilia. If DIES occurs, discontinue Amoxicillin and institute appropriate therapy.

5.4 Clostridioides difficile-Associated Diarrhea (CDAD)

Clostridioidesdifficile-associated diarrhea (CDAD) has been reported with use of nearly all antibacterial agents, including amoxicillin, and may range in severity from mild diarrhea to fatal colitis. Treatment with antibacterial agents alters the normal flora of the colon leading to overgrowth of C. difficile.

C. difficileproduces toxins A and B which contribute to the development of CDAD. Hypertoxin-producing strains of C. difficilecause increased morbidity and mortality, as these infections can be refractory to antimicrobial therapy and may require colectomy. CDAD must be considered in all patients who present with diarrhea following antibacterial use. Careful medical history is necessary since CDAD has been reported to occur over 2 months after the administration of antibacterial agents.

If CDAD is suspected or confirmed, ongoing antibacterial use not directed against C. difficilemay need to be discontinued. Appropriate fluid and electrolyte management, protein supplementation, antibacterial treatment of C. difficile, and surgical evaluation should be instituted as clinically indicated.

5.5 Development of Drug-Resistant Bacteria

Prescribing amoxicillin in the absence of a proven or strongly suspected bacterial infection or prophylactic indication is unlikely to provide benefit to the patient and increases the risk of the development of drug-resistant bacteria.

5.6 Skin Rash in Patients with Mononucleosis

A high percentage of patients with mononucleosis who receive amoxicillin develop an erythematous skin rash. Thus, amoxicillin should not be administered to patients with mononucleosis.

5.7 Phenylketonurics

Aamoxicillin chewable tablets contain aspartame which contains phenylalanine. Each 200 mg chewable tablet contains 1.82 mg phenylalanine; each 400 mg chewable tablet contains 3.64 mg phenylalanine. The oral suspension formulations of Amoxicillin do not contain phenylalanine and can be used by phenylketonurics.

6 ADVERSE REACTIONS

The following are discussed in more detail in other sections of the labeling:

- Anaphylactic reactions [see Warnings and Precautions (5.1)]
- Severe Cutaneous Adverse Reactions [see Warnings and Precautions (5.2)]
- Drug-Induced Enterocolitis Syndrome (DIES) [see Warnings and Precautions (5.3)]
- Clostridioides difficile-Associated Diarrhea (CDAD) [see Warnings and Precautions (5.4)]

6.1 Clinical Trials Experience

Because clinical trials are conducted under widely varying conditions, adverse reaction rates observed in the clinical trials of a drug cannot be directly compared to rates in the clinical trials of another drug and may not reflect the rates observed in practice.

The most common adverse reactions (greater than 1%) observed in clinical trials of amoxicillin tablets or oral suspension were diarrhea, rash, vomiting, and nausea.

Tripletherapy:The most frequently reported adverse events for patients who received triple therapy (amoxicillin/clarithromycin/ lansoprazole) were diarrhea (7%), headache (6%), and taste perversion (5%).

Dualtherapy:The most frequently reported adverse events for patients who received double therapy amoxicillin/lansoprazole were diarrhea (8%) and headache (7%). For more information on adverse reactions with clarithromycin or lansoprazole, refer to the Adverse Reactions section of their package inserts.

6.2 Postmarketing Experience

In addition to adverse events reported from clinical trials, the following events have been identified during postmarketing use of penicillins. Because they are reported voluntarily from a population of unknown size, estimates of frequency cannot be made. These events have been chosen for inclusion due to a combination of their seriousness, frequency of reporting, or potential causal connection to amoxicillin.

- Infectionsand Infestations:Mucocutaneous candidiasis.

- Gastrointestinal: Drug-induced enterocolitis syndrome (DIES), black hairy tongue, and hemorrhagic/pseudomembranous colitis.
- Onset of pseudomembranous colitis symptoms may occur during or after antibacterial treatment [see Warnings and Precautions (5.4)] .

- Immune: Hypersensitivity reactions, anaphylactic/anaphylactoid reactions (including shock), angioedema, serum sickness-like reactions (urticaria or skin rash accompanied by arthritis, arthralgia, myalgia, and frequently fever), hypersensitivity vasculitis [see Warnings and Precautions (5.1)].

- Skin and Appendages:Rashes, pruritus, urticaria, erythema multiforme, SJS, TEN, DRESS, AGEP, exfoliative dermatitis, and linear IgA bullous dermatosis .

- Liver:A moderate rise in AST and/or ALT has been noted, but the significance of this finding is unknown. Hepatic dysfunction including cholestatic jaundice, hepatic cholestasis and acute cytolytic hepatitis have been reported.

- Renal:Crystalluria has been reported [see Overdosage (10)] .

- Hemicand Lymphatic Systems:Anemia, including hemolytic anemia, thrombocytopenia, thrombocytopenic purpura, eosinophilia, leukopenia, and agranulocytosis have been reported .These reactions are usually reversible on discontinuation of therapy and are believed to be hypersensitivity phenomena.

- Central Nervous System:Reversible hyperactivity, agitation, anxiety, insomnia, confusion, convulsions, behavioral changes, aseptic meningitis, and/or dizziness have been reported.

- Miscellaneous:Tooth discoloration (brown, yellow, or gray staining) has been reported. Most reports occurred in pediatric patients. Discoloration was reduced or eliminated with brushing or dental cleaning in most cases.

7 DRUG INTERACTIONS

7.1 Probenecid

Probenecid decreases the renal tubular secretion of amoxicillin. Concurrent use of amoxicillin and probenecid may result in increased and prolonged blood levels of amoxicillin.

7.2 Oral Anticoagulants

Abnormal prolongation of prothrombin time (increased international normalized ratio [INR]) has been reported in patients receiving amoxicillin and oral anticoagulants. Appropriate monitoring should be undertaken when anticoagulants are prescribed concurrently. Adjustments in the dose of oral anticoagulants may be necessary to maintain the desired level of anticoagulation.

7.3 Allopurinol

The concurrent administration of allopurinol and amoxicillin increases the incidence of rashes in patients receiving both drugs as compared to patients receiving amoxicillin alone. It is not known whether this potentiation of rashes is due to allopurinol or the hyperuricemia present in these patients.

7.4 Oral Contraceptives

Amoxicillin may affect the intestinal flora, leading to lower estrogen reabsorption and reduced efficacy of combined oral estrogen/progesterone contraceptives.

7.5 Other Antibacterials

Chloramphenicol, macrolides, sulfonamides, and tetracyclines may interfere with the bactericidal effects of penicillin. This has been demonstrated in vitro; however, the clinical significance of this interaction is not well documented.

7.6 Effects on Laboratory Tests

High urine concentrations of ampicillin may result in false-positive reactions when testing for the presence of glucose in urine using CLINITEST®, Benedict’s Solution, or Fehling’s Solution. Since this effect may also occur with amoxicillin, it is recommended that glucose tests based on enzymatic glucose oxidase reactions (such as CLINISTIX®) be used.

Following administration of ampicillin or amoxicillin to pregnant women, a transient decrease in plasma concentration of total conjugated estriol, estriol-glucuronide, conjugated estrone, and estradiol has been noted.

8 USE IN SPECIFIC POPULATIONS

8.1 Pregnancy

Teratogenic Effects: Pregnancy Category B. Reproduction studies have been performed in mice and rats at doses up to 2000 mg/kg (3 and 6 times the 3 g human dose, based on body surface area). There was no evidence of harm to the fetus due to amoxicillin. There are, however, no adequate and well-controlled studies in pregnant women. Because animal reproduction studies are not always predictive of human response, amoxicillin should be used during pregnancy only if clearly needed.

8.2 Labor and Delivery

Oral ampicillin is poorly absorbed during labor. It is not known whether use of amoxicillin in humans during labor or delivery has immediate or delayed adverse effects on the fetus, prolongs the duration of labor, or increases the likelihood of the necessity for an obstetrical intervention.

8.3 Nursing Mothers

Penicillins have been shown to be excreted in human milk. Amoxicillin use by nursing mothers may lead to sensitization of infants. Caution should be exercised when amoxicillin is administered to a nursing woman.

8.4 Pediatric Use

The safety and effectiveness of AMOXIL for the treatment of upper respiratory tract infections, and infections of the genitourinary tract, skin and skin structure and lower respiratory tract have been established in pediatric patients.

The safety and effectiveness of AMOXIL for the treatment of H.Pyloriinfection have not been established in pediatric patients.

Because of incompletely developed renal function in neonates and young infants, the elimination of amoxicillin may be delayed. Dosing of AMOXIL should be modified in pediatric patients 12 weeks or younger (3 months or younger) [see Dosage and Administration (2.3)].

8.5 Geriatric Use

An analysis of clinical studies of amoxicillin was conducted to determine whether subjects aged 65 and over respond differently from younger subjects. These analyses have not identified differences in responses between the elderly and younger patients, but a greater sensitivity of some older individuals cannot be ruled out.

This drug is known to be substantially excreted by the kidney, and the risk of toxic reactions to this drug may be greater in patients with impaired renal function. Because elderly patients are more likely to have decreased renal function, care should be taken in dose selection, and it may be useful to monitor renal function.

8.6 Dosing in Renal Impairment

Amoxicillin is primarily eliminated by the kidney and dosage adjustment is usually required in patients with severe renal impairment (GFR less than 30 mL/min). See Dosing in Renal Impairment (2.5) for specific recommendations in patients with renal impairment.

10 OVERDOSAGE

In case of overdosage, discontinue amoxicillin, treat symptomatically, and institute supportive measures as required. A prospective study of 51 pediatric patients at a poison-control center suggested that overdosages of less than 250 mg/kg of amoxicillin are not associated with significant clinical symptoms.

Interstitial nephritis resulting in oliguric renal failure has been reported in a small number of patients after overdosage with amoxicillin^1.

Crystalluria, in some cases leading to renal failure, has also been reported after amoxicillin overdosage in adult and pediatric patients. In case of overdosage, adequate fluid intake and diuresis should be maintained to reduce the risk of amoxicillin crystalluria.

Renal impairment appears to be reversible with cessation of drug administration. High blood levels may occur more readily in patients with impaired renal function because of decreased renal clearance of amoxicillin. Amoxicillin may be removed from circulation by hemodialysis.

11 DESCRIPTION

Amoxicillin is a semisynthetic antibacterial, an analog of ampicillin, with a broad spectrum of bactericidal activity against many Gram-positive and Gram-negative microorganisms. Chemically, it is (2 S,5 R,6 R)-6-[(R)-(-)-2-amino-2-(p-hydroxyphenyl)acetamido]-3,3-dimethyl-7-oxo-4-thia-1-azabicyclo[3.2.0]heptane-2-carboxylic acid trihydrate. It may be represented structurally as:

The amoxicillin molecular formula is C16H19N3O5S·3H2O, and the molecular weight is 419.45.

Tablets:Each tablet contains 500 mg or 875 mg amoxicillin as the trihydrate. Each film-coated, capsule-shaped, pink tablet is debossed with AMOXIL centered over 500 or 875, respectively. The 875-mg tablet is scored on the reverse side. Inactive ingredients in each 500 mg or 875 mg tablet: Colloidal silicon dioxide, crospovidone, hypromellose, magnesium stearate, microcrystalline cellulose, polyethylene glycol, sodium starch glycolate, and titanium dioxide.

For Oral Suspension:Each 5 mL of reconstituted suspension contains 200 mg or 400 mg amoxicillin as the trihydrate. Each 5 mL of the 200-mg reconstituted suspension contains 0.15 mEq (3.39 mg) of sodium. Each 5 mL of the 400-mg reconstituted suspension contains 0.19 mEq (4.33 mg) of sodium. Inactive ingredients: flavorings, silica gel, sodium benzoate, sodium citrate, sucrose, and xanthan gum.

Chewable Tablets:Each tablet contains 125 mg or 200 mg or 250 mg or 400 mg of amoxicillin as the trihydrate. Inactive ingredients in each 125 mg or 250 mg chewable tablet: Mannitol, glycine, magnesium stearate, silica gel, flavorings, citric acid, saccharin sodium, and confectioner’s sugar. Inactive ingredients in each 200 mg and 400 mg chewable tablet: Mannitol, crospovidone, flavorings, magnesium stearate, and aspartame [see Warnings and Precautions (5.7) ].

12 CLINICAL PHARMACOLOGY

12.1 Mechanism of Action

Amoxicillin is an antibacterial drug [see Microbiology (12.4)].

12.3 Pharmacokinetics

Absorption: Amoxicillin is stable in the presence of gastric acid and is rapidly absorbed after oral administration. The effect of food on the absorption of amoxicillin from the tablets and suspension of amoxicillin has been partially investigated; 400 mg and 875 mg formulations have been studied only when administered at the start of a light meal.

Orally administered doses of 250 mg and 500 mg amoxicillin capsules result in average peak blood levels 1 to 2 hours after administration in the range of 3.5 mcg/mL to 5.0 mcg/mL and 5.5 mcg/mL to 7.5 mcg/mL, respectively.

Mean amoxicillin pharmacokinetic parameters from an open, two-part, single-dose crossover bioequivalencestudy in 27 adults comparing 875 mg of AMOXICILLIN with 875 mg of AUGMENTIN®(amoxicillian//clavulanate potassium) showed that the 875 mg tablet of AMOXIL produces an AUC0-∞ of 35.4 ± 8.1 mcg•hr/mL and a Cmaxof 13.8 ± 4.1 mcg/mL. Dosing was at the start of a light meal following an overnight fast.

Orally administered doses of amoxicillin suspension, 125 mg/5 mL and 250 mg/5 mL, result in average peak blood levels 1 to 2 hours after administration in the range of 1.5 mcg/mL to 3.0 mcg/mL and 3.5 mcg/mL to 5.0 mcg/mL, respectively.

Oral administration of single doses of 400 mg chewable tablets and 400 mg/5 mL suspension of amoxicillin to 24 adult volunteers yielded comparable pharmacokinetic data:

Table 4: Mean Pharmacokinetic Parameters of AMOXIL (400 mg chewable tablets and 400 mg/5 mL suspension) in Healthy Adults

Dose* | AUC0-∞(mcg·hr/mL) | Cmax(mcg/mL)†
Amoxicillin | Amoxicillin (±S.D.) | Amoxicillin (�S.D.)
400 mg (5 mL of suspension) | 17.1 (3.1) | 5.92 (1.62)
400 mg (1 chewable tablet) | 17.9 (2.4) | 5.18 (1.64)
*Administered at the start of a light meal.
†Mean values of 24 normal volunteers. Peak concentrations occurred approximately 1 hour after the dose.

Distribution: Amoxicillin diffuses readily into most body tissues and fluids, with the exception of brain and spinal fluid, except when meninges are inflamed. In blood serum, amoxicillin is approximately 20% protein-bound. Following a 1-gram dose, and utilizing a special skin window technique to determine levels of the antibiotic, it was noted that therapeutic levels were found in the interstitial fluid.

Metabolism and Excretion: The half-life of amoxicillin is 61.3 minutes. Approximately 60% of an orally administered dose of amoxicillin is excreted in the urine within 6 to 8 hours. Detectable serum levels are observed up to 8 hours after an orally administered dose of amoxicillin. Since most of the amoxicillin is excreted unchanged in the urine, its excretion can be delayed by concurrent administration of probenecid [see Drug Interactions (7.1) ].

12.4 Microbiology

Mechanismof Action

Amoxicillin is similar to penicillin in its bactericidal action against susceptible bacteria during the stage of active multiplication. It acts through the inhibition of cell wall biosynthesis that leads to the death of the bacteria.

Resistance

Resistance to amoxicillin is mediated primarily through enzymes called beta-lactamases that cleave the beta-lactam ring of amoxicillin, rendering it inactive.

Antimicrobial Activity

Amoxicillin has been shown to be active against most isolates of the following microorganisms, both in vitroand in clinical infections [see Indications and Usage (1)] .

Gram-Positive Bacteria

Enterococcusfaecalis

Staphylococcusspp.

Streptococcuspneumoniae

Streptococcusspp. (alpha and beta-hemolytic)

Gram-Negative Bacteria

Escherichiacoli

Haemophilusinfluenzae

Helicobacter pylori

Proteus mirabilis

Susceptibility Test Methods:

For specific information regarding susceptibility test interpretive criteria and associated test methods and quality control standards recognized by FDA for this drug, please see: https://www.fda.gov/STIC .

13 NONCLINICAL TOXICOLOGY

13.1 Carcinogenesis, Mutagenesis, Impairment of Fertility

Long-term studies in animals have not been performed to evaluate carcinogenic potential. Studies to detect mutagenic potential of amoxicillin alone have not been conducted; however, the following information is available from tests on a 4:1 mixture of amoxicillin and potassium clavulanate (AUGMENTIN). AUGMENTIN was non-mutagenic in the Ames bacterial mutation assay, and the yeast gene conversion assay. AUGMENTIN was weakly positive in the mouse lymphoma assay, but the trend toward increased mutation frequencies in this assay occurred at doses that were also associated with decreased cell survival. AUGMENTIN was negative in the mouse micronucleus test and in the dominant lethal assay in mice. Potassium clavulanate alone was tested in the Ames bacterial mutation assay and in the mouse micronucleus test and was negative in each of these assays. In a multi-generation reproduction study in rats, no impairment of fertility or other adverse reproductive effects were seen at doses up to 500 mg/kg (approximately 2 times the 3 g human dose based on body surface area).

14 CLINICAL STUDIES

14.1 H. pyloriEradication to Reduce the Risk of Duodenal Ulcer Recurrence

Randomized, double-blind clinical studies performed in the United States in patients with H. pyloriand duodenal ulcer disease (defined as an active ulcer or history of an ulcer within 1 year) evaluated the efficacy of lansoprazole in combination with amoxicillin capsules and clarithromycin tablets as triple 14-day therapy, or in combination with amoxicillin capsules as dual 14-day therapy, for the eradication of H. pylori. Based on the results of these studies, the safety and efficacy of 2 different eradication regimens were established: Triple therapy:Amoxicillin 1 gram twice daily/clarithromycin 500 mg twice daily/lansoprazole 30 mg twice daily (see Table 5). Dual therapy:Amoxicillin 1 gram three times daily/lansoprazole 30 mg three times daily (see Table 6). All treatments were for 14 days. H. pylorieradication was defined as 2 negative tests (culture and histology) at 4 to 6 weeks following the end of treatment. Triple therapy was shown to be more effective than all possible dual therapy combinations. Dual therapy was shown to be more effective than both monotherapies. Eradication of H. pylorihas been shown to reduce the risk of duodenal ulcer recurrence.

Table 5. H. pyloriEradication Rates When Amoxicillin is Administered as Part of a Triple Therapy Regimen

Study | Triple Therapy | Triple Therapy
Study | Evaluable Analysisa; [95% Confidence Interval]; (number of patients) | Intent-to-Treat Analysisb; [95% Confidence Interval]; (number of patients)
Study 1 | 92; [80.0 to 97.7]; (n equals 48) | 86; [73.3 to 93.5]; (n equals 55)
Study 2 | 86; [75.7 to 93.6]; (n equals 66) | 83; [72.0 to 90.8]; (n equals 70)

aThis analysis was based on evaluable patients with confirmed duodenal ulcer (active or within 1 year) and H. pylori infection at baseline defined as at least 2 of 3 positive endoscopic tests from CLOtest®, histology, and/or culture. Patients were included in the analysis if they completed the study. Additionally, if patients dropped out of the study due to an adverse event related to the study drug, they were included in the analysis as failures of therapy.

bPatients were included in the analysis if they had documented H. pyloriinfection at baseline as defined above and had a confirmed duodenal ulcer (active or within 1 year). All dropouts were included as failures of therapy.

Table 6. H. pyloriEradication Rates When Amoxicillin is Administered as Part of a Dual Therapy Regimen

Study | Dual Therapy | Dual Therapy
Study | Evaluable Analysisa; [95% Confidence Interval]; (number of patients) | Intent-to-Treat Analysisb; [95% Confidence Interval]; (number of patients)
Study 1 | 77; [62.5 to 87.2]; (n equals 51) | 70; [56.8 to 81.2]; (n equals 60)
Study 2 | 66; [51.9 to 77.5]; (n equals 58) | 61; [48.5 to 72.9]; (n equals 67)

aThis analysis was based on evaluable patients with confirmed duodenal ulcer (active or within 1 year) and H. pyloriinfection at baseline defined as at least 2 of 3 positive endoscopic tests from CLOtest®, histology, and/or culture. Patients were included in the analysis if they completed the study. Additionally, if patients dropped out of the study due to an adverse event related to the study drug, they were included in the analysis as failures of therapy.

bPatients were included in the analysis if they had documented H. pyloriinfection at baseline as defined above and had a confirmed duodenal ulcer (active or within 1 year). All dropouts were included as failures of therapy.

15 REFERENCES

1. Swanson-Biearman B, Dean BS, Lopez G, Krenzelok EP. The effects of penicillin and cephalosporin ingestions in children less than six years of age. Vet Hum Toxicol. 1988; 30: 66-67.

16 HOW SUPPLIED/STORAGE AND HANDLING

Amoxicillin for oral suspension, USP: Each 5 mL of reconstituted bubble-gum-flavored suspension contains 400 mg amoxicillin as the trihydrate. The powder for each strength is white to off-white in color and white to off-white when the product is reconstituted.

400 mg/5 mL

NDC 87063-058-50 50-mL bottle (relabeled from NDC 81964-207-50)

NDC 87063-058-75 75-mL bottle (relabeled from NDC 81964-207-51)

NDC 87063-058-01 100-mL bottle (relabeled from NDC 81964-207-52)

Store at or below 25° C (77° F).

Dispense in a tight container.

17 PATIENT COUNSELING INFORMATION

Administration Instructions

Advise patients that amoxicillin may be taken every 8 hours or every 12 hours, depending on the dose prescribed.

Allergic Reactions

Counsel patients that amoxicillin contains a penicillin class drug product that can cause allergic reactions in some individuals.

Severe Cutaneous Adverse Reactions (SCAR)

Advise patients about the signs and symptoms of serious skin manifestations. Instruct patients to stop taking amoxicillin immediately and promptly report the first signs or symptoms of skin rash, mucosal lesions, or any other sign of hypersensitivity [see Warnings and Precautions (5.2)] .

Diarrhea

Counsel patients that diarrhea is a common problem caused by antibacterial drugs which usually ends when the antibacterial drug is discontinued. Sometimes after starting treatment with antibacterial drugs, patients can develop watery and bloody stools (with or without stomach cramps and fever) even as late as 2 or more months after having taken their last dose of the antibacterial drug. If this occurs, patients should contact their physician as soon as possible.

Antibacterial Resistance

Patients should be counseled that antibacterial drugs, including amoxicillin, should only be used to treat or prevent bacterial infections. Antibacterial drugs do not treat viral infections (e.g., the common cold). When amoxicillin is prescribed to treat a bacterial infection, patients should be told that although it is common to feel better early in the course of therapy, the medication should be taken exactly as directed. Skipping doses or not completing the full course of therapy may: (1) decrease the effectiveness of the immediate treatment, and (2) increase the likelihood that bacteria will develop resistance and will not be treatable by amoxicillin or other antibacterial drugs in the future.

Storage Instructionsand Special Handling Instruction

It is preferable to refrigerate amoxicillin suspensions, but not required. Shake oral suspensions well before each use. Keep bottle tightly closed. When dosing a child with the suspension (liquid), use a calibrated oral syringe. Be sure to rinse the calibrated oral syringe after each use. Bottles of suspension of amoxicillin may contain more liquid than required. Follow your doctor’s instructions about the amount to use and the days of treatment your child requires. Discard any unused portion of the suspension after 14 days.

Phenylketonuria

Counsel patients with phenylketonuria: Each 200 mg chewable tablet contains 1.82 mg phenylalanine; each 400 mg chewable tablet contains 3.64 mg phenylalanine.

Relabeled by:

Enovachem PHARMACEUTICALS

Torrance, CA 90501

CLINITEST is a registered trademark of Miles, Inc.

CLINISTIX is a registered trademark of Bayer Corporation.

CLOtest is a registered trademark of Kimberly-Clark Corporation.

AMOXIL is a registered trademark of GlaxoSmithKline and is licensed to USAntibiotics, LLC.

AUGMENTIN is a registered trademark of GlaxoSmithKline and is licensed to USAntibiotics, LLC.